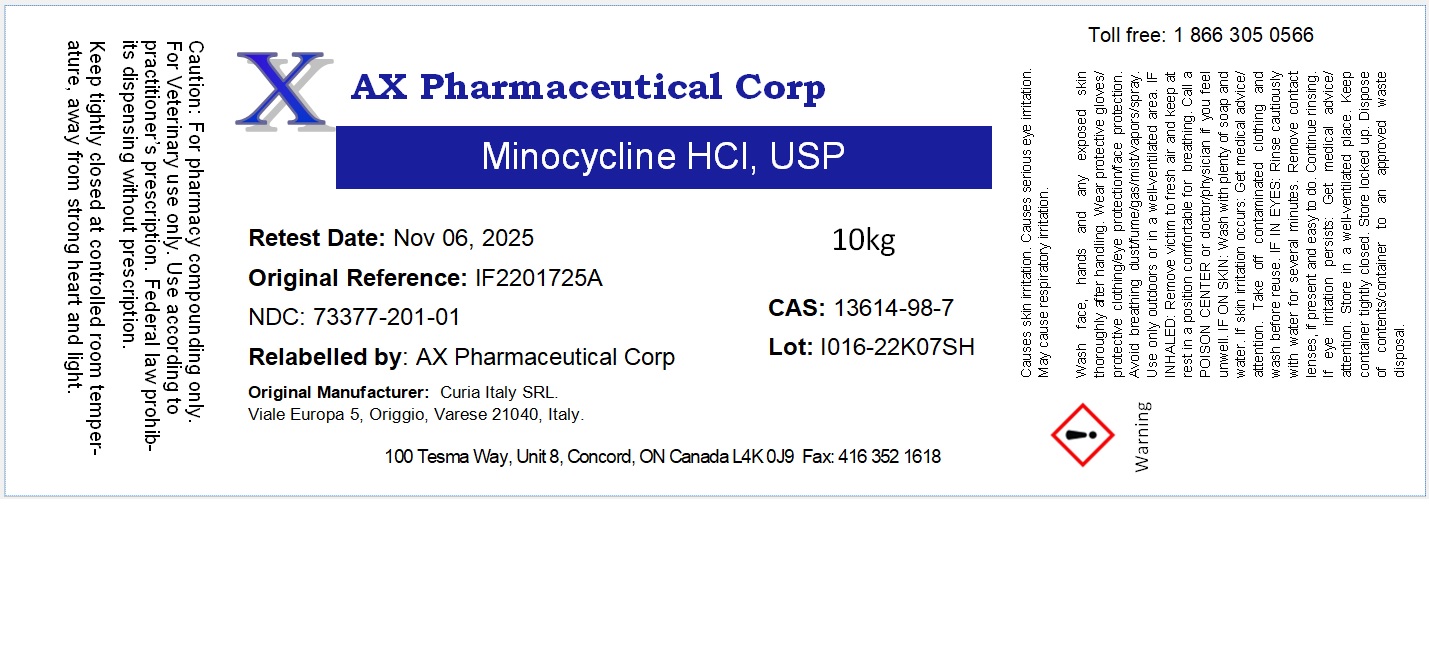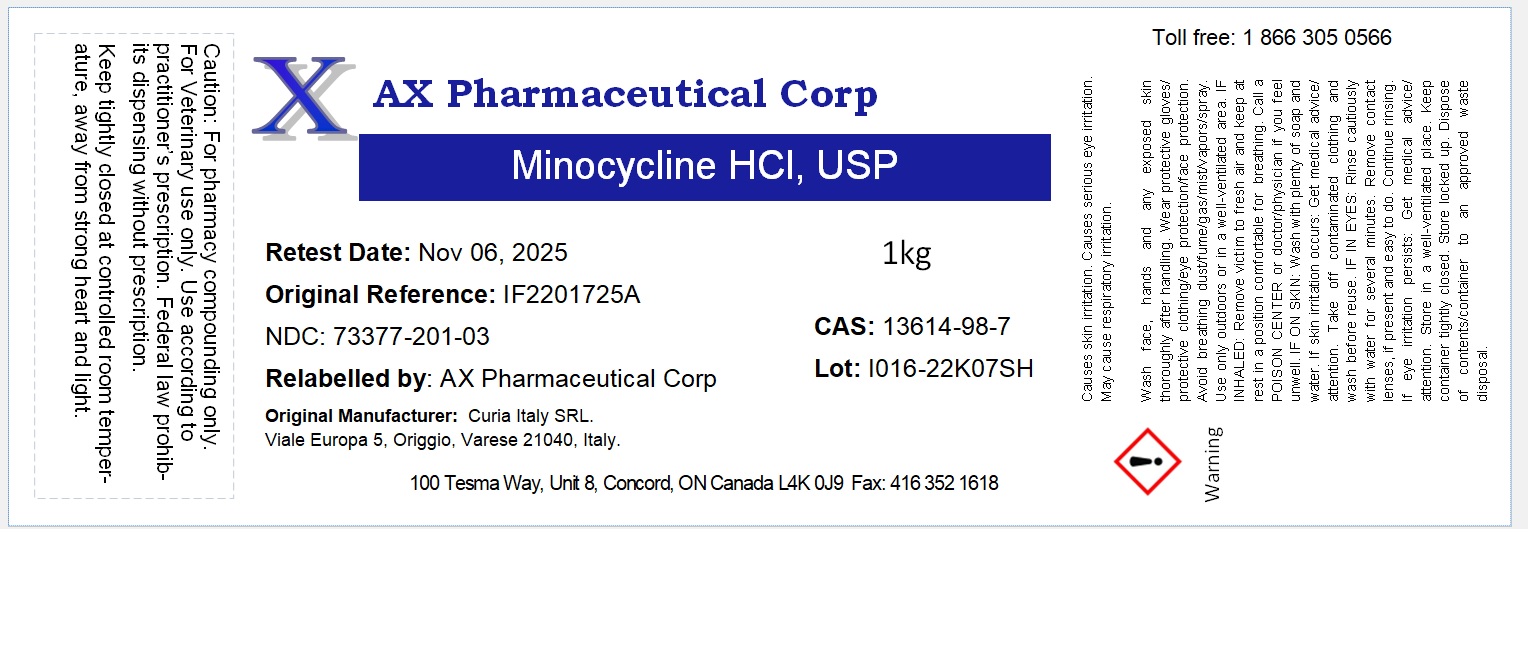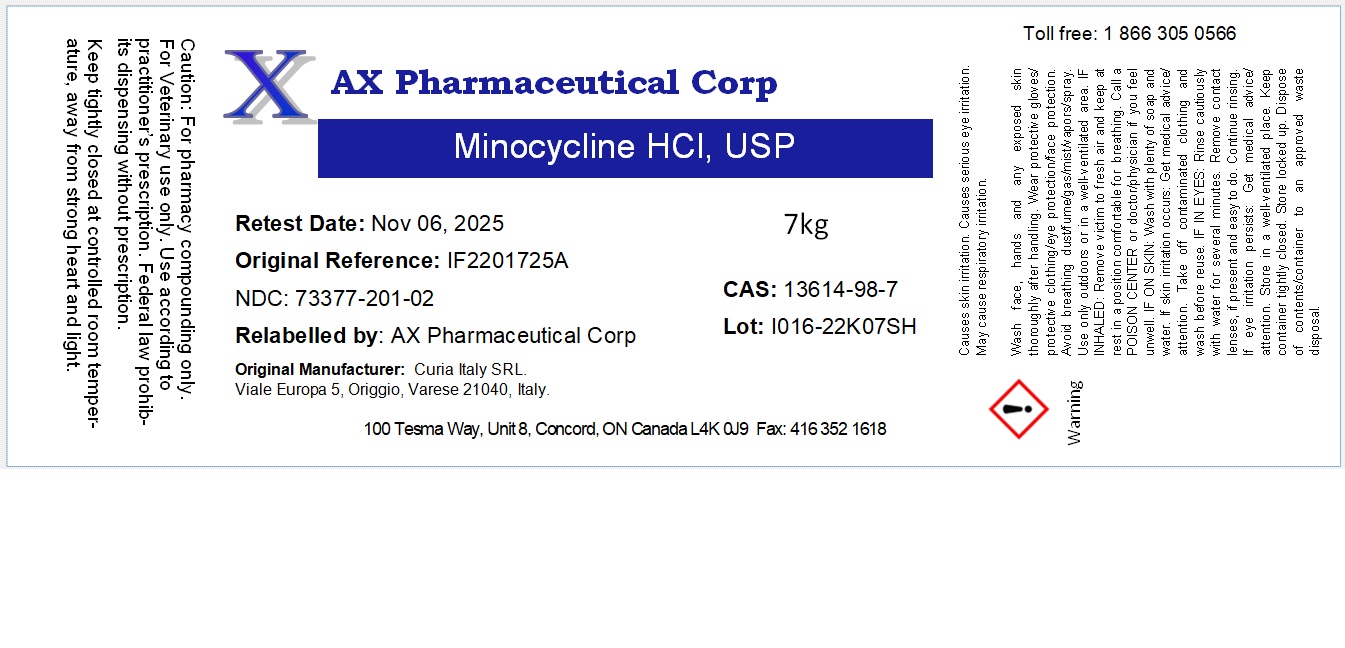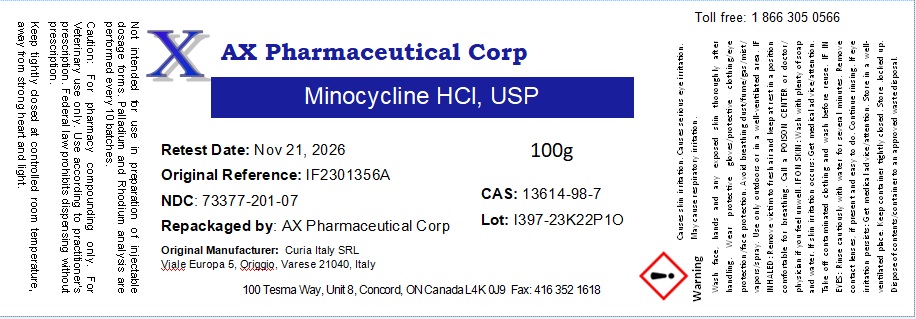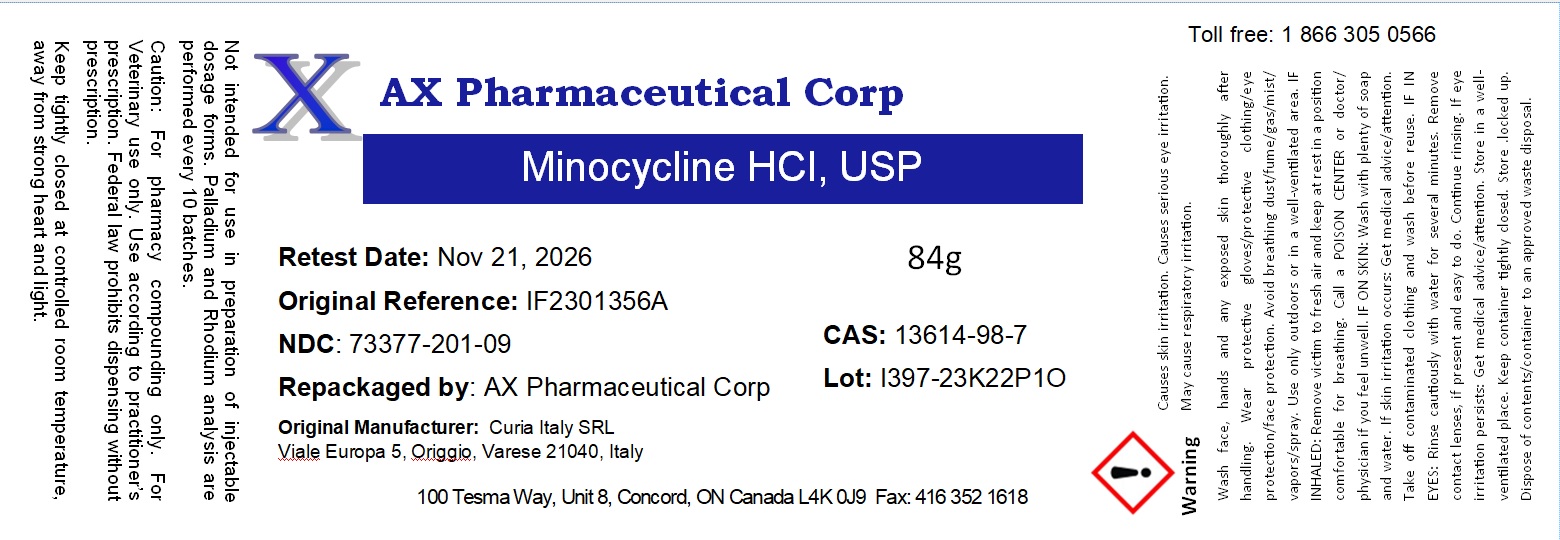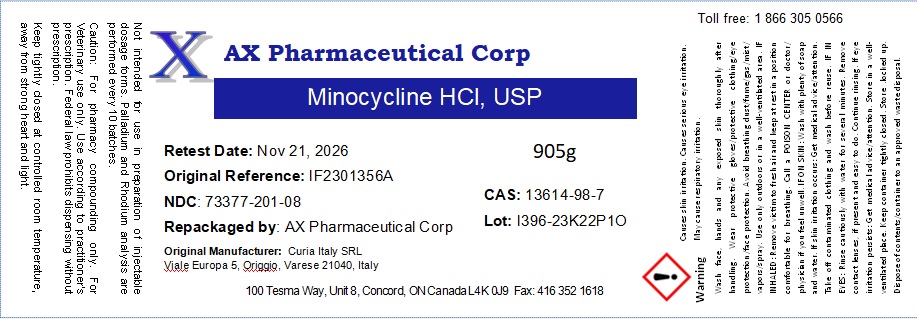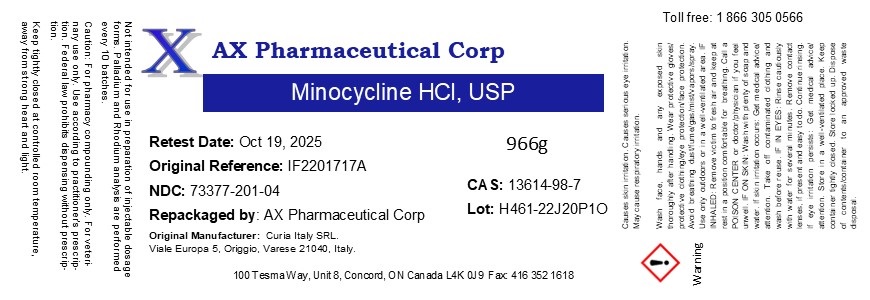 DRUG LABEL: Minocycline HCl
NDC: 73377-201 | Form: POWDER
Manufacturer: AX Pharmaceutical Corp
Category: other | Type: BULK INGREDIENT - ANIMAL DRUG
Date: 20240205

ACTIVE INGREDIENTS: MINOCYCLINE HYDROCHLORIDE 1 g/1 g

Minocycline HCl